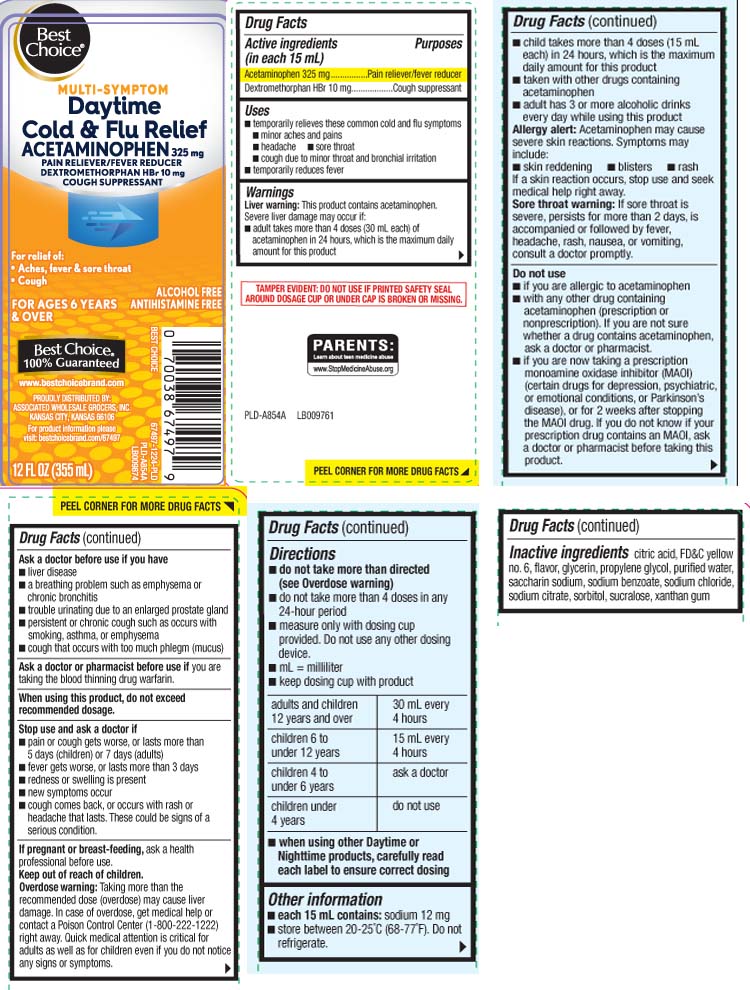 DRUG LABEL: Cold and Flu Relief
NDC: 63941-291 | Form: LIQUID
Manufacturer: Best Choice  (Valu Merchandisers Company)
Category: otc | Type: HUMAN OTC DRUG LABEL
Date: 20260224

ACTIVE INGREDIENTS: ACETAMINOPHEN 325 mg/15 mL; DEXTROMETHORPHAN HYDROBROMIDE 10 mg/15 mL
INACTIVE INGREDIENTS: ANHYDROUS CITRIC ACID; FD&C YELLOW NO. 6; GLYCERIN; PROPYLENE GLYCOL; WATER; SACCHARIN SODIUM; TRISODIUM CITRATE DIHYDRATE; SODIUM BENZOATE; SODIUM CHLORIDE; SORBITOL; SUCRALOSE; XANTHAN GUM

Drug Facts

Active ingredients (in each 15 mL)

Acetaminophen 325 mg

Dextromethoprhan HBr 10 mg

Purposes

Pain reliever/fever reducer

Cough suppressant

Uses

- temporarily relieves these common cold/flu symptoms:
  - minor aches and pains
  - headache
  - sore throat
  - cough due to minor throat and bronchial irritation
- temporarily reduces fever

Warnings

Liver warning: This product contains acetaminophen. Severe liver damage may occur if you take:

- adult takes more than 4 doses (30 mL each) of acetaminophen in 24 hours, which is the maximum daily amount
- child takes more than 4 doses (15 mL each) in 24 hours, which is the maximum daily amount for this product
- taken with other drugs containing acetaminophen
- adult has 3 or more alcoholic drinks everyday while using this product

Allery alert: Acetaminophen may cause severe skin reactions. Symptoms may include:

- skin reddening
- blisters
- rash

If a skin reaction occurs, stop use and seek medical help right away

Sore throat warning: If sore throat is severe, persists for more than 2 days, is accompanied or followed by fever, headache, rash, nausea, or vomiting, consult a doctor promptly.

Do not use

- if you are allergic to acetaminophen
- with any other drug containing acetaminophen (prescription or nonprescription). If you are not sure whether a drug contains acetaminophen, ask a doctor or pharmacist
- if you are now taking a prescription monoamine oxidase inhibitor (MAOI) (certain drugs for depression, psychiatric, or emotional conditions, or Parkinson's disease) or for 2 weeks after stopping the MAOI drug. If you do not know if your prescription drug contains an MAOI, ask a doctor or pharmacist before taking this product.

Ask a doctor before use if you have

- liver disease
- a breathing problem such as emphysema or chronic bronchitis
- trouble urinating due to an enlarged prostate gland
- persistent or chronic cough such as occurs with smoking, asthma or emphysema
- cough that occurs by excessive phlegm (mucus)

Ask a doctor or pharmacist before use if the user is

taking the blood thinning drug warfarin.

When using this product,

do not exceed recommended dosage.

Stop use and ask a doctor if

- pain, or cough gets worse or lasts more than 5 days (children) or 7 days (adults)
- fever gets worse, or lasts more more than 3 days
- redness or swelling is present
- new symptoms occur
- cough comes back, or occurs with rash or headache that lasts.

These could be signs of a serious condition.

If pregnant or breast-feeding,

ask a health professional before use.

Keep out of reach of children.

Overdose warning: Taking more than the recommended dose (overdose) may cause liver damage. In case of overdose, get medical help or contact a Poison Control Center (1-800-222-1222) right away. Quick medical attention is critical for adults as well as for children even if you do not notice any signs or symptoms.

Directions

- do not take more than directed (see overdose warning)
- do not take more than 4 doses in any 24-hour period
- measure only with dosing cup provided. Do not use any other dosing device
- keep dosing cup with product
- mL=milliliter

adults and children 12 years and over | 30 mL every 4 hours
children 6 to under 12 years | 15 mL every 4 hours
children 4 to under 6 years | ask a doctor
children under 4 years | do not use

- When using Daytime or Nighttime products, carefully read each label to ensure correct dosing

Other information

- each 15 mL contains: sodium 12 mg
- store between 20-25ºC (68-77ºF). Do not refrigerate

Inactive ingredients

citric acid, FD&C yellow #6, flavor, glycerin, propylene glycol, purified water, saccharin sodium, sodium benzoate, sodium chloride, sodium citrate, sorbitol, sucralose, xanthan gum

Questions or comments?

Call

Principal Display Panel

MULTI-SYMPTOM

Daytime

Cold & Flu Relief

ACETAMINOPHEN 325 mg

PAIN RELIEVER/FEVER REDUCER

DEXTROMETHORPHAN HBr 10 mg

COUGH SUPPRESSANT

For relief of:

- Aches, fever & sore throat
- Cough

FOR AGES 6 YEARS & OVER

ALCOHOL FREE

ANTIHISTAMINEFREE

FL OZ (mL)

TAMPER EVIDENT: DO NOT USE IF PRINTED SAFETY SEAL AROUND DOSAGE CUP OR UNDER CAP IS BROKEN OR MISSING.

*This product is not manufactured or distributed by The Procter & Gamble Company.Vicks® and DayQuil® are registered trademarks of The Procter & Gamble Company.

DISTRIBUTED BY:

ASSOCIATED WHOLESALE GROCERS, INC.

KANSAS CITY, KANSAS 66106

Package Label

BEST CHOICE Multi-Symptom Daytime Cold & Flu Relief